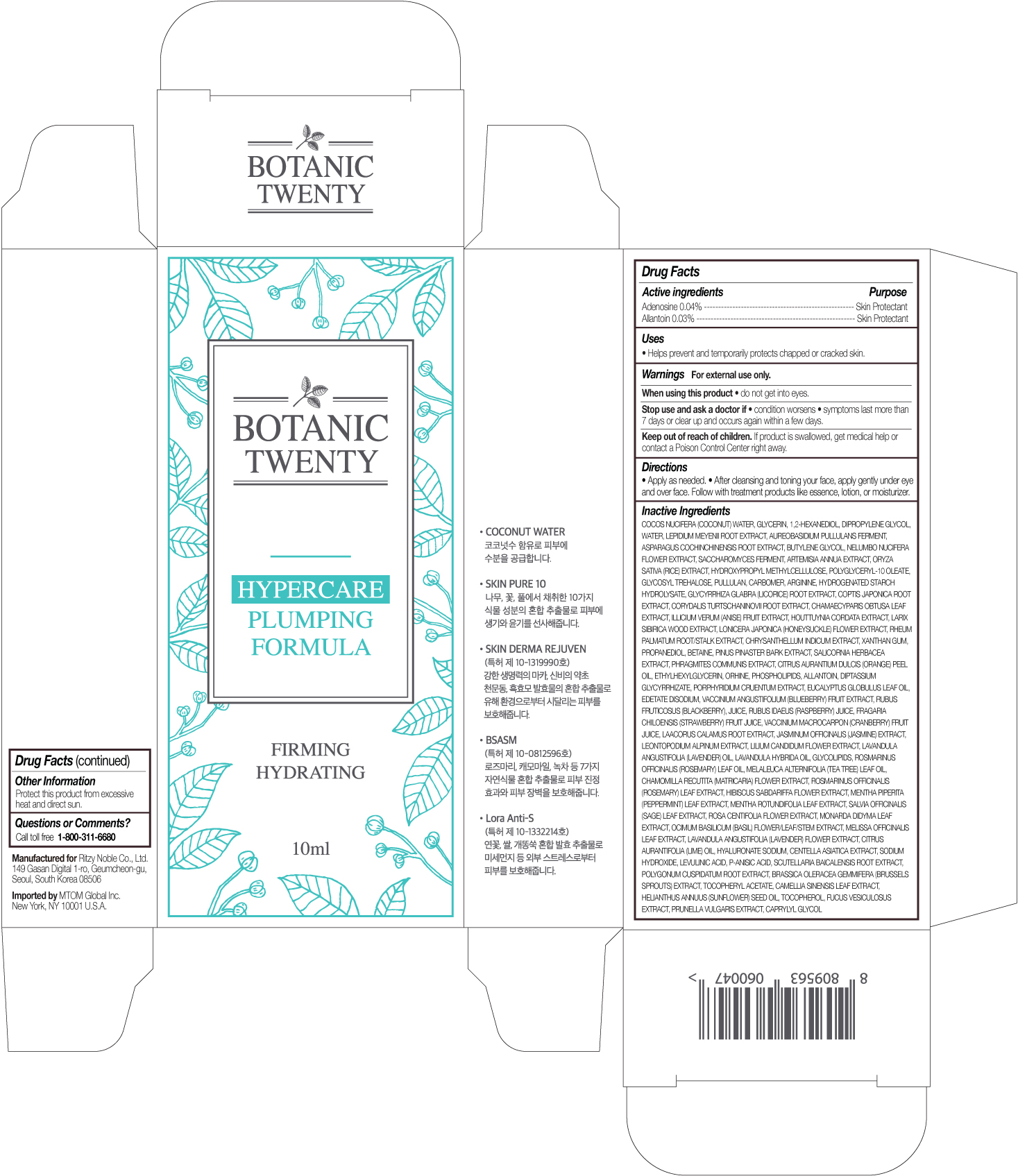 DRUG LABEL: BOTANIC TWENTY HYPERCARE PLUMPING FORMULA
NDC: 71364-100 | Form: LIQUID
Manufacturer: RITZY NOBLE CO., LTD.
Category: otc | Type: HUMAN OTC DRUG LABEL
Date: 20180101

ACTIVE INGREDIENTS: ADENOSINE 0.04 g/10 mL; ALLANTOIN 0.03 g/10 mL
INACTIVE INGREDIENTS: COCONUT WATER; HYPROMELLOSES; POLYGLYCERYL-10 OLEATE; TREHALOSE; PROPANEDIOL; ORNITHINE; EGG PHOSPHOLIPIDS; ACORUS CALAMUS ROOT; SALVIA OFFICINALIS WHOLE; ROSA CENTIFOLIA FLOWER; MONARDA DIDYMA LEAF; GLYCYRRHIZINATE DIPOTASSIUM; PORPHYRIDIUM PURPUREUM; VACCINIUM ANGUSTIFOLIUM WHOLE; RUBUS FRUTICOSUS WHOLE; RUBUS IDAEUS WHOLE; FRAGARIA CHILOENSIS WHOLE; VACCINIUM MACROCARPON WHOLE; JASMINUM OFFICINALE FLOWER; HIBISCUS SABDARIFFA FLOWER; MENTHA PIPERITA LEAF; OCIMUM BASILICUM WHOLE; MELISSA OFFICINALIS LEAF; SODIUM HYDROXIDE; LEVULINIC ACID; P-ANISIC ACID; BRASSICA OLERACEA VAR. GEMMIFERA WHOLE; HELIANTHUS ANNUUS SEED WAX; TOCOPHEROL; FUCUS VESICULOSUS; PRUNELLA VULGARIS; PULLULAN; BETAINE; 1,2-HEXANEDIOL; DIPROPYLENE GLYCOL; NELUMBO NUCIFERA FLOWER; ARTEMISIA ANNUA WHOLE; SACCHAROMYCES LYSATE; BAMBUSA VULGARIS SAP; HYALURONIC ACID; BIFIDOBACTERIUM LONGUM; COPTIS JAPONICA ROOT; CHAMAECYPARIS OBTUSA LEAF; RHEUM PALMATUM ROOT; BUTYLENE GLYCOL; LEPIDIUM MEYENII ROOT; AUREOBASIDIUM PULLULANS VAR. PULLUTANS; WATER; GLYCERIN; LONICERA JAPONICA FLOWER; CHRYSANTHEMUM INDICUM FLOWER; CORYDALIS TURTSCHANINOVII WHOLE; ILLICIUM VERUM WHOLE; LARIX SIBIRICA WOOD; YEAST MANNAN; BEE PROPOLIS EXTRACT; ETHYLHEXYLGLYCERIN; CITRUS AURANTIUM FRUIT OIL; CENTELLA ASIATICA; EUCALYPTUS GLOBULUS LEAF; ACETYL GLUTAMIC ACID; LECITHIN, SOYBEAN; LAVANDULA ANGUSTIFOLIA FLOWER; LAVANDULA X INTERMEDIA FLOWER; PINUS PINASTER WOOD; POLYGONUM CUSPIDATUM ROOT; SCUTELLARIA BAICALENSIS ROOT; ROSMARINUS OFFICINALIS FLOWERING TOP OIL; MELALEUCA ALTERNIFOLIA LEAF; .ALPHA.-TOCOPHEROL ACETATE; MATRICARIA CHAMOMILLA FLOWERING TOP; MALTODEXTRIN; POTASSIUM SORBATE; ROSMARINUS OFFICINALIS WHOLE; BELLIS PERENNIS FLOWER; FREESIA ALBA FLOWER; LEONTOPODIUM ALPINUM; LILIUM CANDIDUM FLOWER; MORUS ALBA BARK; PANAX GINSENG ROOT WATER; CAMELLIA SINENSIS WHOLE; CHRYSANTHEMUM X MORIFOLIUM FLOWER; MAGNOLIA LILIIFLORA FLOWER; MENTHA X ROTUNDIFOLIA LEAF; NELUMBO NUCIFERA LEAF; PUNICA GRANATUM SEED; EDETATE DISODIUM; SODIUM POLYACRYLATE (2500000 MW); KONJAC MANNAN; SAUSSUREA INVOLUCRATA FLOWERING TOP; BACILLUS POLYFERMENTICUS; CAPRYLYL GLYCOL; FOLIC ACID; HEXAPEPTIDE-11; OLIGOPEPTIDE-10; ASPARAGUS COCHINCHINENSIS WHOLE; HYDROXYETHYL UREA; XANTHAN GUM; HOUTTUYNIA CORDATA TOP; ORYZA SATIVA WHOLE; SORBITOL; ALOE VERA LEAF; GLYCYRRHIZA GLABRA; POLYSORBATE 80; CARBOMER 940; ARGININE; HYDROGENATED STARCH HYDROLYSATE; PHRAGMITES AUSTRALIS WHOLE; SALICORNIA DEPRESSA WHOLE; LAVANDULA ANGUSTIFOLIA WHOLE

ACTIVE INGREDIENTS

ADENOSINE 0.04%

ALLANTOIN 0.03%

PURPOSE

SKIN PROTECTANT

USES

Helps prevent and temporarily protects chapped or cracked skin.

WARNINGS

FOR EXTERNAL USE ONLY

WHEN USING THIS PRODUCT

• do not get into eyes.

STOP USE AND ASK A DOCTOR IF

• condition worsens

• symptoms last more than 7 days or clear up and occurs again within a few days.

KEEP OUT OF REACH OF CHILDREN

If product is swallowed, get medical help or contact a Poison Control Center right away.

DIRECTIONS

• Apply as needed.

• After cleansing and toning your face, apply gently under eye and over face. Follow with treatment products like essence, lotion, or moisturizer.

INACTIVE INGREDIENTS

COCOS NUCIFERA (COCONUT) WATER, GLYCERIN, 1,2-HEXANEDIOL, DIPROPYLENE GLYCOL, WATER, LEPIDIUM MEYENII ROOT EXTRACT, AUREOBASIDIUM PULLULANS FERMENT, ASPARAGUS COCHINCHINENSIS ROOT EXTRACT, BUTYLENE GLYCOL, NELUMBO NUCIFERA FLOWER EXTRACT, SACCHAROMYCES FERMENT, ARTEMISIA ANNUA EXTRACT, ORYZA SATIVA (RICE) EXTRACT, HYDROXYPROPYL METHYLCELLULOSE, POLYGLYCERYL-10 OLEATE, GLYCOSYL TREHALOSE, PULLULAN, CARBOMER, ARGININE, HYDROGENATED STARCH HYDROLYSATE, GLYCYRRHIZA GLABRA (LICORICE) ROOT EXTRACT, COPTIS JAPONICA ROOT EXTRACT, CORYDALIS TURTSCHANINOVII ROOT EXTRACT, CHAMAECYPARIS OBTUSA LEAF EXTRACT, ILLICIUM VERUM (ANISE) FRUIT EXTRACT, HOUTTUYNIA CORDATA EXTRACT, LARIX SIBIRICA WOOD EXTRACT, LONICERA JAPONICA (HONEYSUCKLE) FLOWER EXTRACT, RHEUM PALMATUM ROOT/STALK EXTRACT, CHRYSANTHELLUM INDICUM EXTRACT, XANTHAN GUM, PROPANEDIOL, BETAINE, PINUS PINASTER BARK EXTRACT, SALICORNIA HERBACEA EXTRACT, PHRAGMITES COMMUNIS EXTRACT, CITRUS AURANTIUM DULCIS (ORANGE) PEEL OIL, ETHYLHEXYLGLYCERIN, ORHINE, PHOSPHOLIPIDS, ALLANTOIN, DIPTASSIUM GLYCYRRHIZATE, PORPHYRIDIUM CRUENTUM EXTRACT, EUCALYPTUS GLOBULUS LEAF OIL, EDETATE DISODIUM, VACCINIUM ANGUSTIFOLIUM (BLUEBERRY) FRUIT EXTRACT, RUBUS FRUTICOSUS (BLACKBERRY), JUICE, RUBUS IDAEUS (RASPBERRY) JUICE, FRAGARIA CHILOENSIS (STRAWBERRY) FRUIT JUICE, VACCINIUM MACROCARPON (CRANBERRY) FRUIT JUICE, LAACORUS CALAMUS ROOT EXTRACT, JASMINUM OFFICINALIS (JASMINE) EXTRACT, LEONTOPODIUM ALPINUM EXTRACT, LILIUM CANDIDUM FLOWER EXTRACT, LAVANDULA ANGUSTIFOLIA (LAVENDER) OIL, LAVANDULA HYBRIDA OIL, GLYCOLIPIDS, ROSMARINUS OFFICINALIS (ROSEMARY) LEAF OIL, MELALEUCA ALTERNIFOLIA (TEA TREE) LEAF OIL, CHAMOMILLA RECUTITA (MATRICARIA) FLOWER EXTRACT, ROSMARINUS OFFICINALIS (ROSEMARY) LEAF EXTRACT, HIBISCUS SABDARIFFA FLOWER EXTRACT, MENTHA PIPERITA (PEPPERMINT) LEAF EXTRACT, MENTHA ROTUNDIFOLIA LEAF EXTRACT, SALVIA OFFICINALIS (SAGE) LEAF EXTRACT, ROSA CENTIFOLIA FLOWER EXTRACT, MONARDA DIDYMA LEAF EXTRACT, OCIMUM BASILICUM (BASIL) FLOWER/LEAF/STEM EXTRACT, MELISSA OFFICINALIS LEAF EXTRACT, LAVANDULA ANGUSTIFOLIA (LAVENDER) FLOWER EXTRACT, CITRUS AURANTIFOLIA (LIME) OIL, HYALURONATE SODIUM, CENTELLA ASIATICA EXTRACT, SODIUM HYDROXIDE, LEVULINIC ACID, P-ANISIC ACID, SCUTELLARIA BAICALENSIS ROOT EXTRACT, POLYGONUM CUSPIDATUM ROOT EXTRACT, BRASSICA OLERACEA GEMMIFERA (BRUSSELS SPROUTS) EXTRACT, TOCOPHERYL ACETATE, CAMELLIA SINENSIS LEAF EXTRACT, HELIANTHUS ANNUUS (SUNFLOWER) SEED OIL, TOCOPHEROL, FUCUS VESICULOSUS EXTRACT, PRUNELLA VULGARIS EXTRACT, CAPRYLYL GLYCOL

OTHER INFORMATION

Protect this product from excessive heat and direct sun.

QUESTIONS OR COMMENTS?

Call toll free 1-800-311-6680